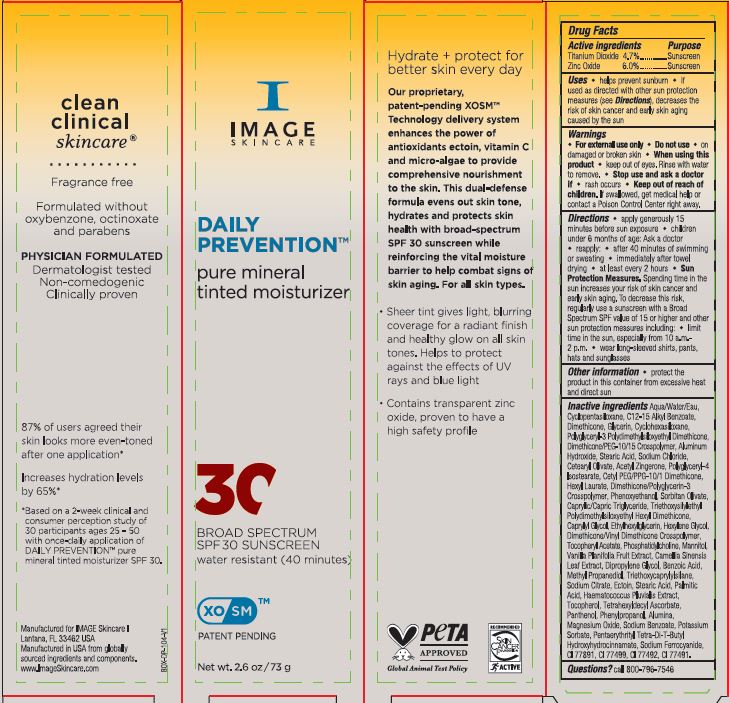 DRUG LABEL: Daily Prevention Pure Mineral Tinted Moisturizer SPF 30
NDC: 62742-4254 | Form: CREAM
Manufacturer: Allure Labs
Category: otc | Type: HUMAN OTC DRUG LABEL
Date: 20240315

ACTIVE INGREDIENTS: TITANIUM DIOXIDE 4.7 g/100 g; ZINC OXIDE 6 g/100 g
INACTIVE INGREDIENTS: ACETYL ZINGERONE; POLYGLYCERYL-4 ISOSTEARATE; SORBITAN OLIVATE; PENTAERYTHRITOL TETRAKIS(3-(3,5-DI-TERT-BUTYL-4-HYDROXYPHENYL)PROPIONATE); POTASSIUM SORBATE; FERROSOFERRIC OXIDE; FERRIC OXIDE YELLOW; ETHYLHEXYLGLYCERIN; TOCOPHEROL; PHENOXYETHANOL; CAPRYLYL GLYCOL; CYCLOMETHICONE 6; BENZOIC ACID; PHENYLPROPANOL; MAGNESIUM OXIDE; SODIUM FERROCYANIDE; DIMETHICONE; SODIUM CHLORIDE; WATER; CETEARYL OLIVATE; CETYL PEG/PPG-10/1 DIMETHICONE (HLB 4); HEXYL LAURATE; MEDIUM-CHAIN TRIGLYCERIDES; GREEN TEA LEAF; DIPROPYLENE GLYCOL; MANNITOL; METHYLPROPANEDIOL; ECTOINE; PALMITIC ACID; FERRIC OXIDE RED; DIMETHICONE/PEG-10/15 CROSSPOLYMER; SODIUM CITRATE; HAEMATOCOCCUS PLUVIALIS; ALUMINUM OXIDE; HEXYLENE GLYCOL; STEARIC ACID; ALUMINUM HYDROXIDE; TRIETHOXYSILYLETHYL POLYDIMETHYLSILOXYETHYL HEXYL DIMETHICONE; .ALPHA.-TOCOPHEROL ACETATE; TETRAHEXYLDECYL ASCORBATE; PANTHENOL; VANILLA; TRIETHOXYCAPRYLYLSILANE; SODIUM BENZOATE; CYCLOMETHICONE 5; ALKYL (C12-15) BENZOATE; GLYCERIN; DIMETHICONE/VINYL DIMETHICONE CROSSPOLYMER (SOFT PARTICLE); PHOSPHATIDYLCHOLINE TRANSLOCATOR ABCB4; DIMETHICONE/POLYGLYCERIN-3 CROSSPOLYMER; POLYGLYCERYL-3 POLYDIMETHYLSILOXYETHYL DIMETHICONE (4000 MPA.S)

Drug Facts

Active ingredients

Titanium Dioxide 4.7%

Zinc Oxide 6.0%

Purpose: Sunscreen

INDICATIONS AND USAGE

Uses • helps prevent sunburn • if used as directed with other sun protection measures (see Directions), decreases the risk of skin cancer and early skin aging caused by the sun.

Warnings • For external use only

Do not use • on damaged or broken skin

When using this product • keep out of eyes. Rinse with water to remove.

Stop use and ask a doctor if • rash occurs

DOSAGE AND ADMINISTRATION

Directions • apply generously 15 minutes before sun exposure • children under 6 months of age: Ask a doctor • reapply: • after 40 minutes of swimming or sweating • immediately after towel drying • at least every 2 hours • Sun Protection Measures. Spending time in the sun increases your risk of skin cancer and early skin aging. To decrease this risk, regularly use a sunscreen with a Broad Spectrum SPF value of 15 or higher and other sun protection measures including: • limit time in the sun, especially from 10 a.m.-2 p.m. • wear long-sleeved shirts, pants, hats and sunglasses.

Keep out of reach of children. if swallowed, get medical help or contact a Poison Control Center right away.

Other information • protect the product in this container from excessive heat and direct sun

INACTIVE INGREDIENT

Inactive ingredients: Agua/Water/Eau, Cyclopentasiloxane, C12-15 Alkyl Benzoate, Dimethicone, Glycerin, Cyclohexasiloxane, Polyglyceryl-3 Polydimethylsiloxyethyl Dimethicone, Dimethicone /PEG-10/15 Crosspolymer, Aluminum Hydroxide, Stearic Acid, Sodium Chloride, Cetearyl Olivate, Acetyl Zingerone, PolyglyceryI-4 lsostearate, Cetyl PEG/PPG-10/1 Dimethicone, Hexyl Laurate, Dimethicone/Polyglycerin-3 Crosspolymer, Phenoxyethanol, Sorbitan Oliveto, Caprylic/Capric Triglyceride, Triethoxysilyethyl Polydimethylsiloxyethyl Hexyl Dimethicone, Caprylyl Glycol, Ethylhexylglycerin, Hexylene Glycol, Dimethicone/Vinyl Dimethicone Crosspolymer, Tocopheryl Acetate, Phosphatidylcholine, Mannitol, Vanilla Planifolia Fruit Extract, Camellia Sinensis Leaf Extract, Dipropylene Glycol, Benzoic Acid, Methyl Propanediol, Triethoxycapryiyisilane, Sodium Citrate, Ectoin, Stearic Acid, Palmitic Acid, Haematococcus Pluvialis Extract, Tocopherol, Tatrahexyldecyl Ascorbate, Panthenol, Phenylpropanol, Alumina, Magnesium Oxide, Sodium Benzoate, Potassium Sorbate, Pentaerythrityl Tetra-Di-T-Butyl Hydroxyhydrocinnamate, Sodium Ferrocyanide, CI 77891, CI 77499, CI 77492, CI 77491.